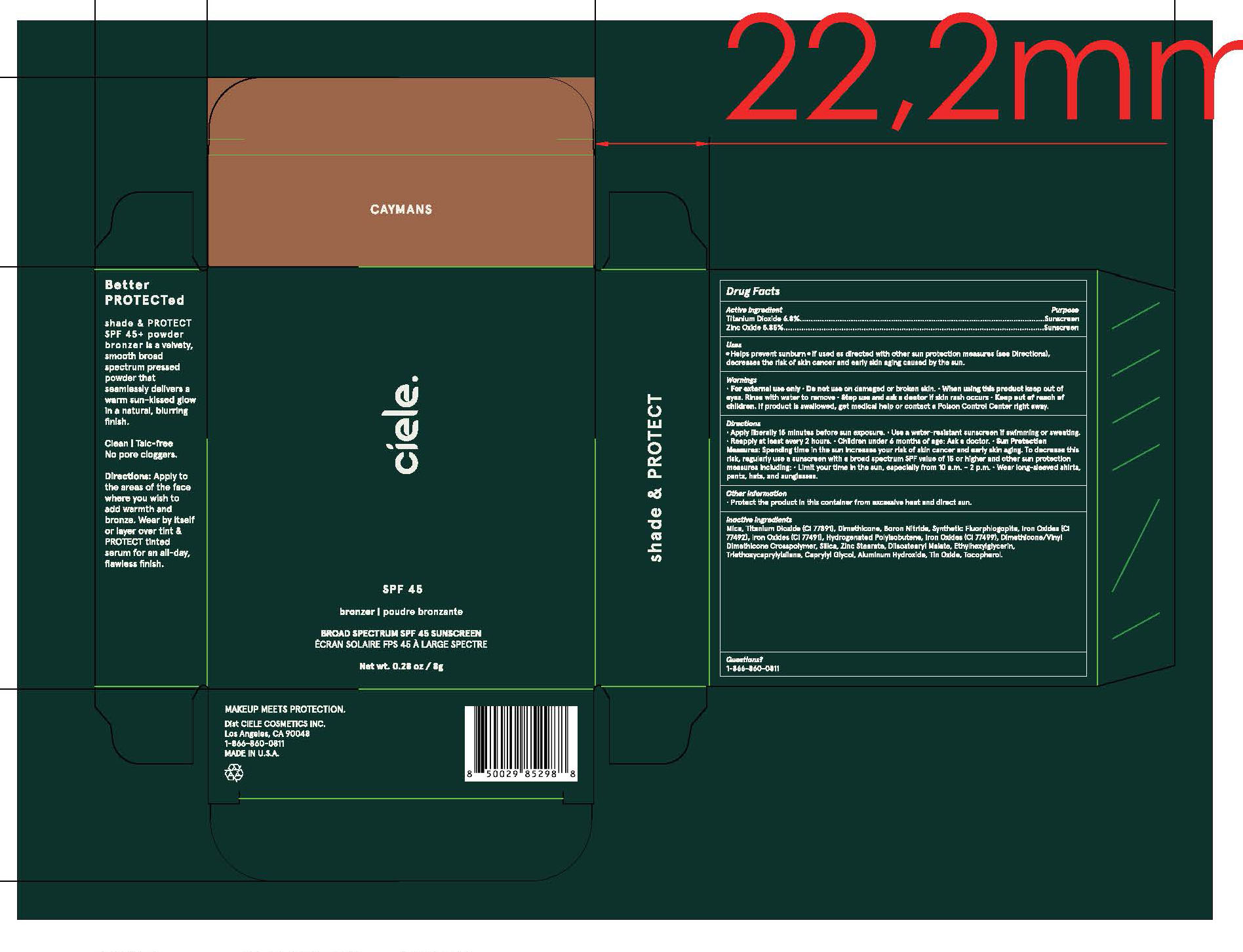 DRUG LABEL: Ceile shade PROTECT Broad Spectrum SPF 45 Sunscreen Caymans
NDC: 83103-4200 | Form: CREAM
Manufacturer: LÚE COSMETICS INC
Category: otc | Type: HUMAN OTC DRUG LABEL
Date: 20260127

ACTIVE INGREDIENTS: TITANIUM DIOXIDE 6.8 mg/100 mg; ZINC OXIDE 5.85 mg/100 mg
INACTIVE INGREDIENTS: MICA; BORON NITRIDE; HYDROGENATED POLYISOBUTENE (1300 MW); DIMETHICONE/VINYL DIMETHICONE CROSSPOLYMER (SOFT PARTICLE); SILICON DIOXIDE; ZINC STEARATE; DIISOSTEARYL MALATE; ETHYLHEXYLGLYCERIN; TRIETHOXYCAPRYLYLSILANE; DIMETHICONE; CAPRYLYL GLYCOL; ALUMINUM HYDROXIDE; TIN OXIDE; TOCOPHEROL; BROWN IRON OXIDE

Ceile shade PROTECT Broad Spectrum SPF 45 Sunscreen Caymans

Active Ingredients

Titanium Dioxid 6.8%

Zinc Oxide 5.85%

Uses

● helps prevent sunburn
● if used as directed with other sun protection measures (see Directions),
decreases the risk of skin cancer and early skin aging caused by the sun

Warnings

For external use only
Do not use on damaged or broken skin.
When using this product keep out of eyes. Rinse with water to remove.
Stop use and ask a docor if rash occurs
Keep out of reach of children. If swallowed, get medical help or contact a Poison Control Center right away.

Directions

•apply generously 15 minutes before sun exposure and as needed
• reapply at least every 2 hours.

• use a water resistant sunscreen if swimming or sweating
• Sun Protection Measures. Spending time in the sun

increases your risk of skin cancer and early skin aging. To decrease
this risk, regularly use a sunscreen with a Broad Spectrum SPF
value of 15 or higher and other sun protection measures including:
• limit time in the sun, especially from 10 a.m. - 2 p.m.
• wear long-sleeved shirts, pants, hats, and sunglasses
• children under 6 months of age: Ask a doctor

Inactive ingredients

Mica, Dimethicone, Boron Nitride, Synthetic Fluorphlogopite, Hydrogenated Polyisobutene, Dimethicone/Vinyl Dimethicone Crosspolymer, Silica, Zinc Stearate, Diisostearyl Malate, Ethylhexylglycerin, Triethoxycaprylylsilane, Caprylyl Glycol, Aluminum Hydroxide, Tin Oxide, Tocopherol, CI 77891 (Titanium Dioxide), CI 77491, CI 77492, CI 77499 (Iron Oxides).

Other Information

Protect the product in this container from excessive heat and direct sun.

Questions?

1-866-860-0811

Purpose

Sunscreen

Keep out of reach of children